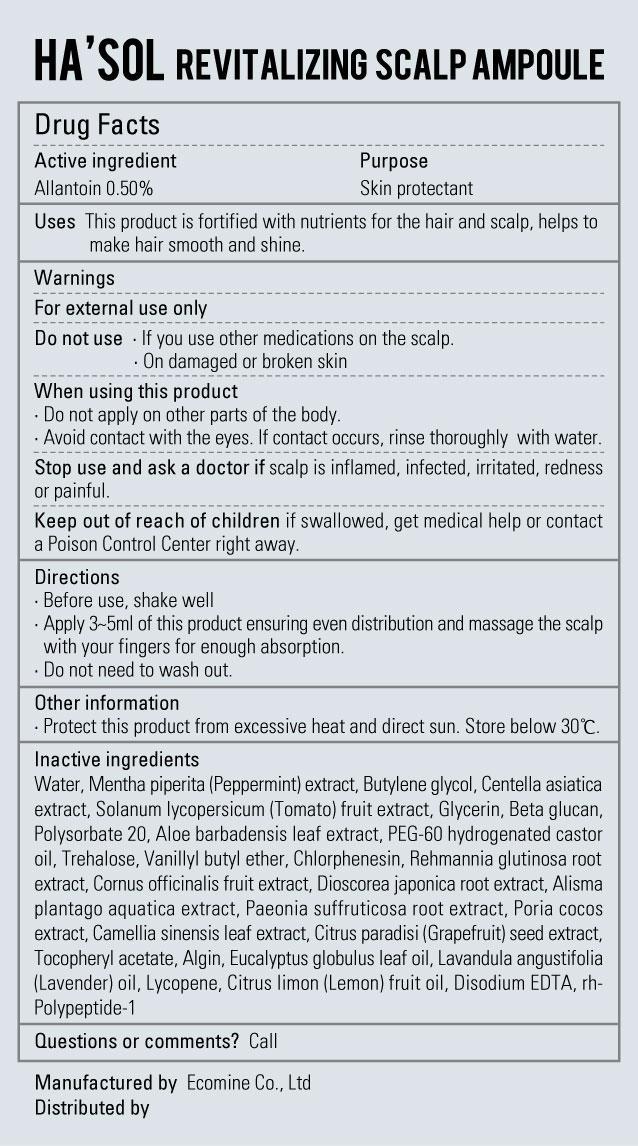 DRUG LABEL: Hasol Revitalizing Scalp Ampoule
                
NDC: 51270-116 | Form: LIQUID
Manufacturer: Ecomine Co Ltd
Category: otc | Type: HUMAN OTC DRUG LABEL
Date: 20130701

ACTIVE INGREDIENTS: ALLANTOIN 0.1 g/10 g
INACTIVE INGREDIENTS: WATER; MENTHA PIPERITA; BUTYLENE GLYCOL; CENTELLA ASIATICA; TOMATO; GLYCERIN; POLYSORBATE 20; ALOE VERA LEAF; PEG-60 HYDROGENATED CASTOR OIL; TREHALOSE; VANILLYL BUTYL ETHER; CHLORPHENESIN; REHMANNIA GLUTINOSA ROOT; CORNUS OFFICINALIS FRUIT; DIOSCOREA JAPONICA TUBER; ALISMA PLANTAGO-AQUATICA TOP; PAEONIA SUFFRUTICOSA ROOT; FU LING; GREEN TEA LEAF; CITRUS PARADISI SEED; .ALPHA.-TOCOPHEROL ACETATE; SODIUM ALGINATE; EUCALYPTUS OIL; LAVENDER OIL; LYCOPENE; CITRUS LIMON FRUIT OIL; EDETATE DISODIUM

Hasol Revitalizing Scalp Ampoule

Drug Facts

Active Ingredient

Allantoin 0.50%

Purpose

Skin protectant

Keep out of Reach of Children

Stop use and ask a doctor if scalp is inflamed, infected, irritated, redness or painful.

Keep out of reach of children if swallowed, get medical help or contact a Poison Control Center right away.

Indication & Usage

Directions
■ Before use, shake well
■ Apply 3~5ml of this product ensuring even distribution and massage the scalp with your fingers for enough absorption.
■ Do not need to wash out.

Warnings

For external use only

Do not use ■ If you use other medications on the scalp.
■ On damaged or broken skin

When using this product
■ Do not apply on other parts of the body
■ Avoid contact with the eyes. If contact occurs, rinse thoroughly with water.

Dosage & Administration

Uses ■ This product is fortified with nutrients for the hair and scalp, helps to make hair smooth and shine.

Inactive ingredients

Water, Mentha piperita (Peppermint) extract, Butylene glycol, Centella asiatica extract, Solanum lycopersicum (Tomato) fruit extract, Glycerin, Beta glucan, Polysorbate 20, Aloe barbadensis leaf extract, PEG-60 hydrogenated castor oil, Trehalose, Vanillyl butyl ether, Chlorphenesin, Rehmannia glutinosa root extract, Cornus officinalis fruit extract, Dioscorea japonica root extract, Alisma plantago aquatica extract, Paeonia suffruticosa root extract, Poria cocos extract, Camellia sinensis leaf extract, Citrus paradisi (Grapefruit) seed extract, Tocopheryl acetate, Algin, Eucalyptus globulus leaf oil, Lavandula angustifolia (Lavender) oil, Lycopene, Citrus limon (Lemon) fruit oil, Disodium EDTA, rh-Polypeptide-1

Hasol Revitalizing Scalp Ampoule

Net WT. 0.35FL OZ(10ml) * 12EA